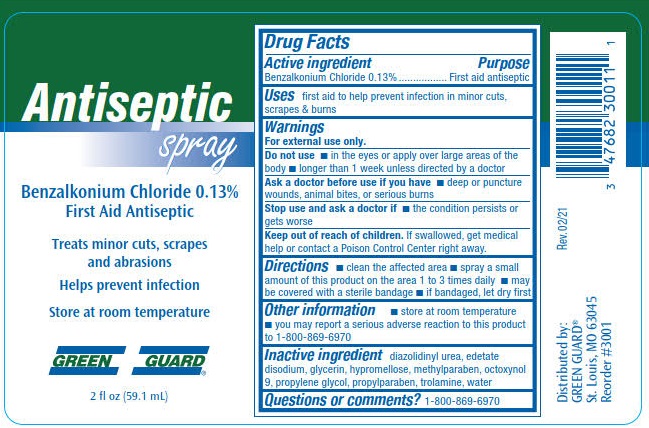 DRUG LABEL: Green Guard Antiseptic
NDC: 47682-317 | Form: SPRAY
Manufacturer: Unifirst First Aid Corporation
Category: otc | Type: HUMAN OTC DRUG LABEL
Date: 20240117

ACTIVE INGREDIENTS: BENZALKONIUM CHLORIDE 1.3 g/1 L
INACTIVE INGREDIENTS: GLYCERIN; METHYLPARABEN; OCTOXYNOL 9; DIAZOLIDINYL UREA; EDETATE DISODIUM; TROLAMINE; WATER; PROPYLPARABEN; HYPROMELLOSE, UNSPECIFIED; PROPYLENE GLYCOL

Green Guard Antiseptic Spray

Drug Facts

Active ingredient

Benzalkonium Chloride 0.13%

Purpose

First aid antiseptic

Uses

first aid to help prevent infection in minor cuts, scrapes & burns

Warnings

For external use only.

Do not use

- in the eyea or apply over large areas of the body
- longer than 1 week unless directed by a doctor

Ask a doctor before use if you have

- deep or puncture wounds, animal bites, or serious burns

Stop use and ask a doctor if

- the condition persists or gets worse

Keep out of reach of children.

If swallowed, get medical help or contact a Poison Control Center right away.

Directions

- clean the affected area
- spray a small amount of this product on the area 1 to 3 times daily
- may be covered by a sterile bandage
- if bandaged, let dry first

Other information

- store at room temperature
- you may report a serious adverse reaction to this product to 1-800-869-6970

Inactive ingredients

diazolidinyl urea, edetate disodium, glycerin, hypromellose, methylparaben, octoxynol 9, propylene glycol, propylparaben, trolamine, water

Questions or comments? 1-800-869-6970

PACKAGE LABEL

Antiseptic Spray
Benzalkonium Chloride 0.13%
First Aid Antiseptic
Treats minor cuts, scrapes and abrasions

Helps prevent infection

Store at room temperature

Green Guard®

2 fl oz (59.1 mL)